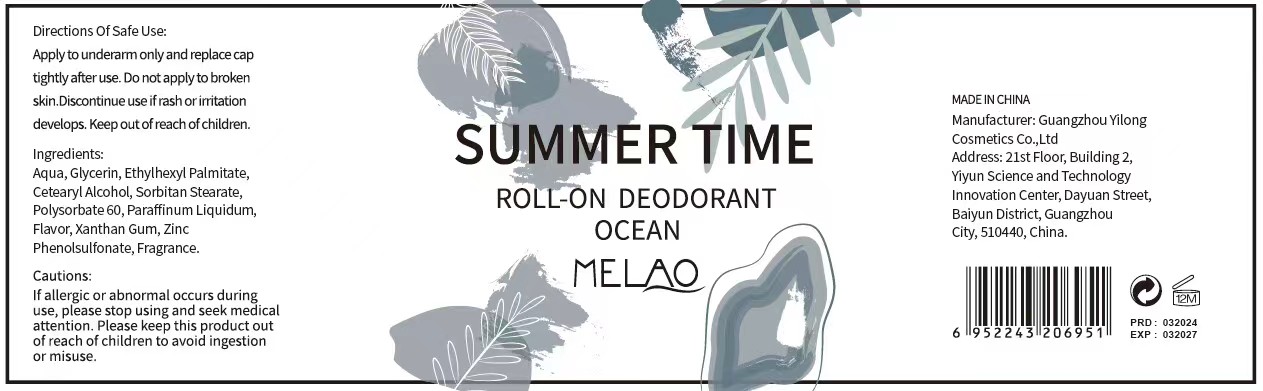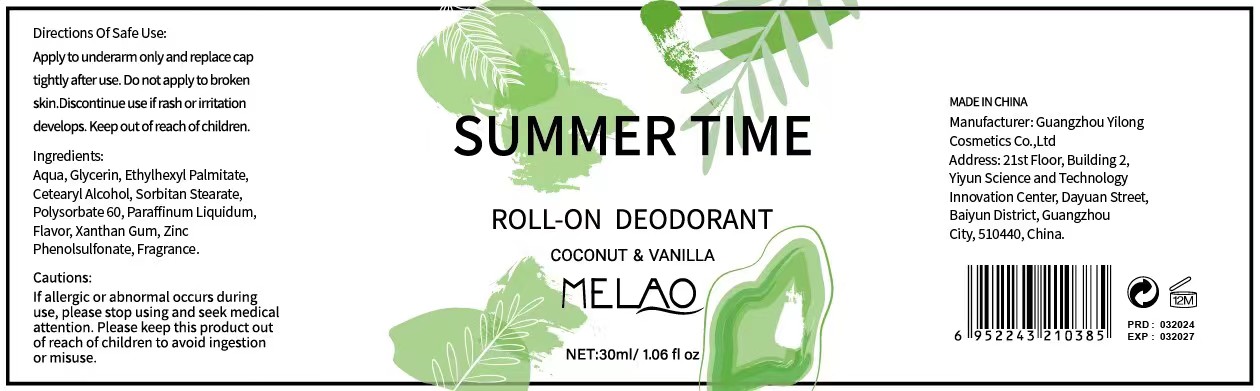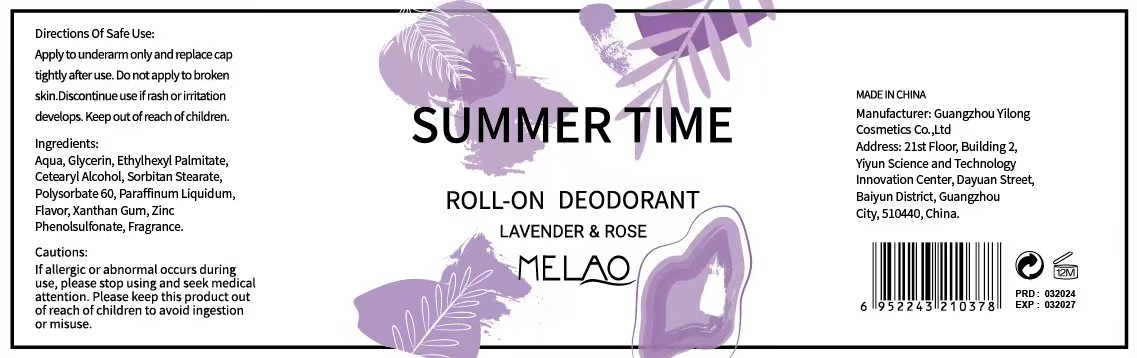 DRUG LABEL: MELAO Roll-on Deodorant
NDC: 83566-295 | Form: LIQUID
Manufacturer: Guangzhou Yilong Cosmetics Co.,Ltd.
Category: otc | Type: HUMAN OTC DRUG LABEL
Date: 20240603

ACTIVE INGREDIENTS: ZINC PHENOLSULFONATE 2 mg/100 mL
INACTIVE INGREDIENTS: PARAFFIN; CETYL ALCOHOL; PEG-6 SORBITAN STEARATE; POLYSORBATE 60; WATER O-15; GLYCERIN; ETHYLHEXYL PALMITATE; XANTHAN GUM

MELAO Roll-on Deodorant

Active ingredients

Zinc Phenolsulfonate 2%

Purpose

Deodorant

Uses

Apply to underarm only and replace cap tightly after use.

WARNINGS

For external use only.

Stop use and ask a doctor if

rash occurs

Do not use

on damaged or broken skin.

When using this product

keep out of eyes. Rinse with water to remove.

Keep out of reach of children.

If swallowed, get medical help or contact a Poison Control Center right away.

INACTIVE INGREDIENT

PARAFFIN
CETYL ALCOHOL
PEG-6 SORBITAN STEARATE
POLYSORBATE 60
WATER O-15

GLYCERIN
ETHYLHEXYL PALMITATE
XANTHAN GUM

DOSAGE AND ADMINISTRATION

Apply to underarm only and replace cap tightly after use.
Do not apply to broken skin.Discontinue use if rash or irritation develops. Keep out
of reach of children.